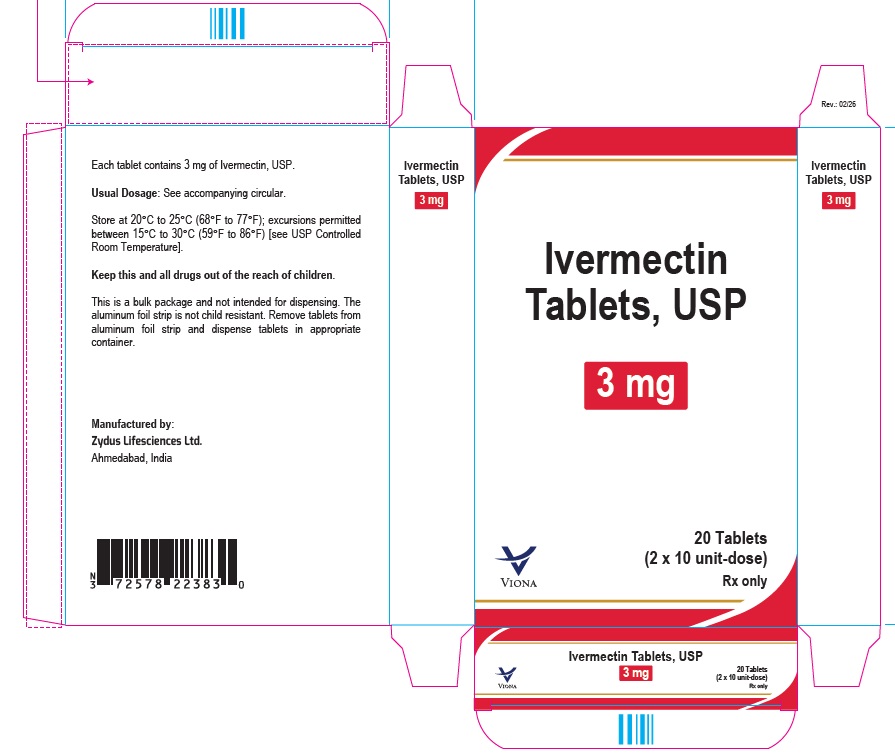 DRUG LABEL: Ivermectin
NDC: 70771-1731 | Form: TABLET
Manufacturer: Zydus Lifesciences Limited
Category: prescription | Type: HUMAN PRESCRIPTION DRUG LABEL
Date: 20260227

ACTIVE INGREDIENTS: IVERMECTIN 3 mg/1 1
INACTIVE INGREDIENTS: CROSCARMELLOSE SODIUM; FERRIC OXIDE RED; HYPROMELLOSE 2910 (3 MPA.S); MAGNESIUM STEARATE; MICROCRYSTALLINE CELLULOSE 101; STARCH, CORN

Ivermectin Tablets, USP

PACKAGE LABEL.PRINCIPAL DISPLAY PANEL

NDC 70771-1731-3

Ivermectin Tablets USP, 3 mg

Cartons of 20 (2 x 10) unit-dose tablets

Rx only